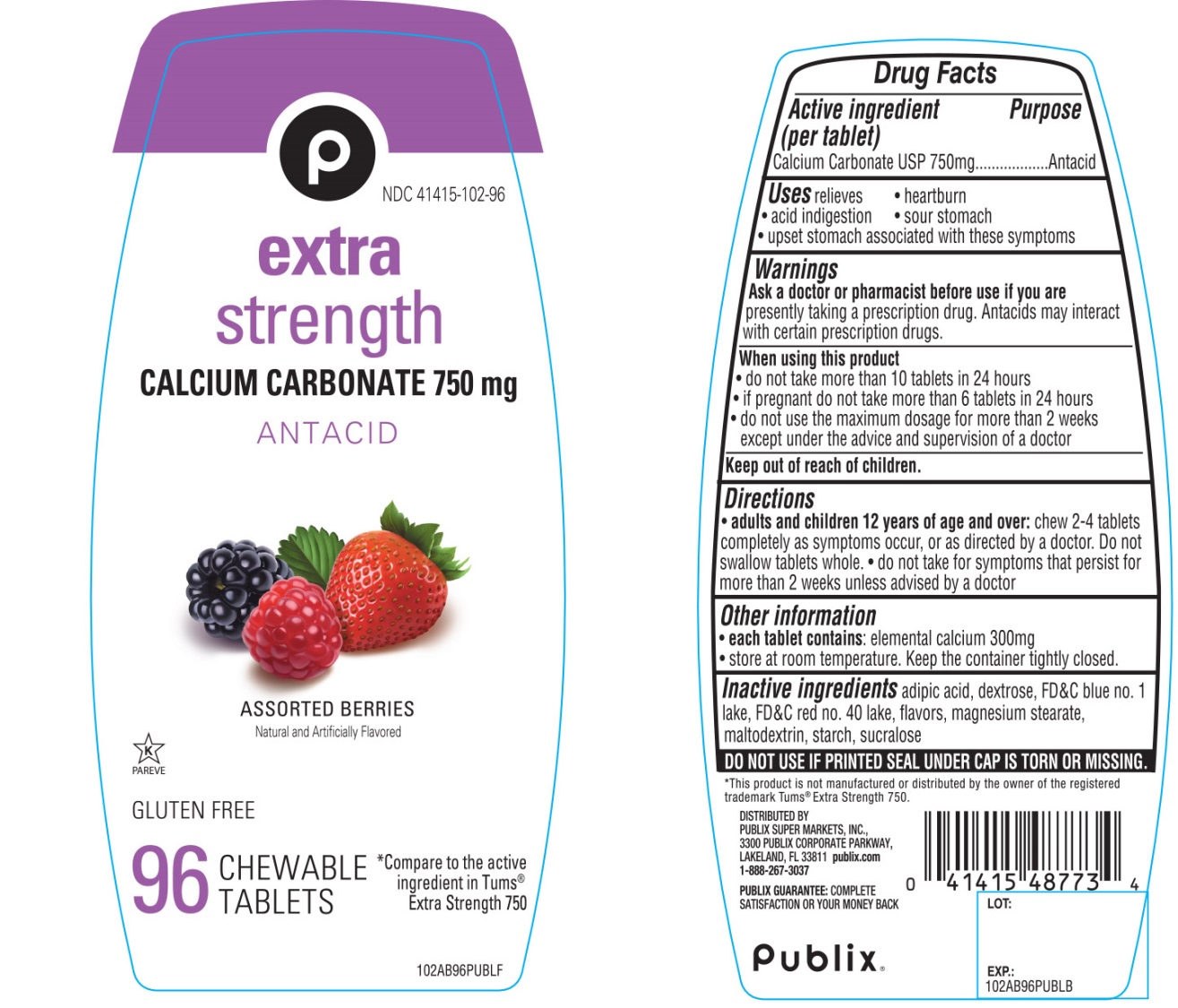 DRUG LABEL: Publix Extra Strength

NDC: 41415-102 | Form: TABLET, CHEWABLE
Manufacturer: PUBLIX SUPER MARKETS, INC
Category: otc | Type: HUMAN OTC DRUG LABEL
Date: 20251028

ACTIVE INGREDIENTS: CALCIUM CARBONATE 750 mg/1 1
INACTIVE INGREDIENTS: ADIPIC ACID; DEXTROSE, UNSPECIFIED FORM; FD&C BLUE NO. 1; FD&C RED NO. 40; MAGNESIUM STEARATE; MALTODEXTRIN; STARCH, CORN; SUCRALOSE

Publix®Extra Strength Assorted Berries 96 Chewable Tablets

Active ingredient (per tablet)

Calcium Carbonate USP 750mg

Purpose

Antacid

Uses

relieves

- heartburn
- acid indigestion
- sour stomach
- upset stomach associated with these symptoms

Warnings

Ask a doctor or pharmacist before use if you arepresently taking a prescription drug. Antacids may interact with certain prescription drugs.

When using this product

- do not take more than 10 tablets in 24 hours
- If pregnant do not take more than 6 tablets in 24 hours
- do not use the maximum dosage for more than 2 weeks except under the advice and supervision of a doctor

Directions

- adults and children 12 years of age and over:chew 2-4 tablets as symptoms occur or as directed by a doctor. Do not swallow tablets whole.
- do not take for symptoms that persist for more than 2 weeks unless advised by a doctor.

Other Information

- each tablet contains: elemental calcium 300mg
- store at room temperature. Keep the container tightly closed.

Inactive ingredients

adipic acid, dextrose, FD&C blue #1 lake, FD&C red #40 lake, flavors, magnesium stearate, maltodextrin, starch, sucralose.

Questions or comments?

1-866-467-2748

SAFETY SEALED: DO NOT USE IF PRINTED SEAL UNDER CAP IS TORN OR MISSING

Package/Label Principal Display Panel

Publix®

NDC# 41415-102-96

Compare to the active ingredient in Tums®Extra Strength 750

Assorted Berries Flavor

EXTRA STRENGTH

CALCIUM CARBONATE 750 mg

ANTACID

ASSORTED BERRIES

Natural and Artificially Flavored

96 CHEWABLE TABLETS

K PAREVE

GLUTEN-FREE

DISTRIBUTED BY:

PUBLIX SUPER MARKETS, INC.,

3300 PUBLIX CORPORATE PARKWAY,

LAKELAND, FL 33811 publix.com

1-888-267-3037

PUBLIX GUARANTEE: COMPLETE SATISFACTION GUARANTEE OR YOUR MONEY BACK

*This product is not manufactured or distributed by GlaxoSmithKline, the owner of the registered trademark Tums®Extra Strength